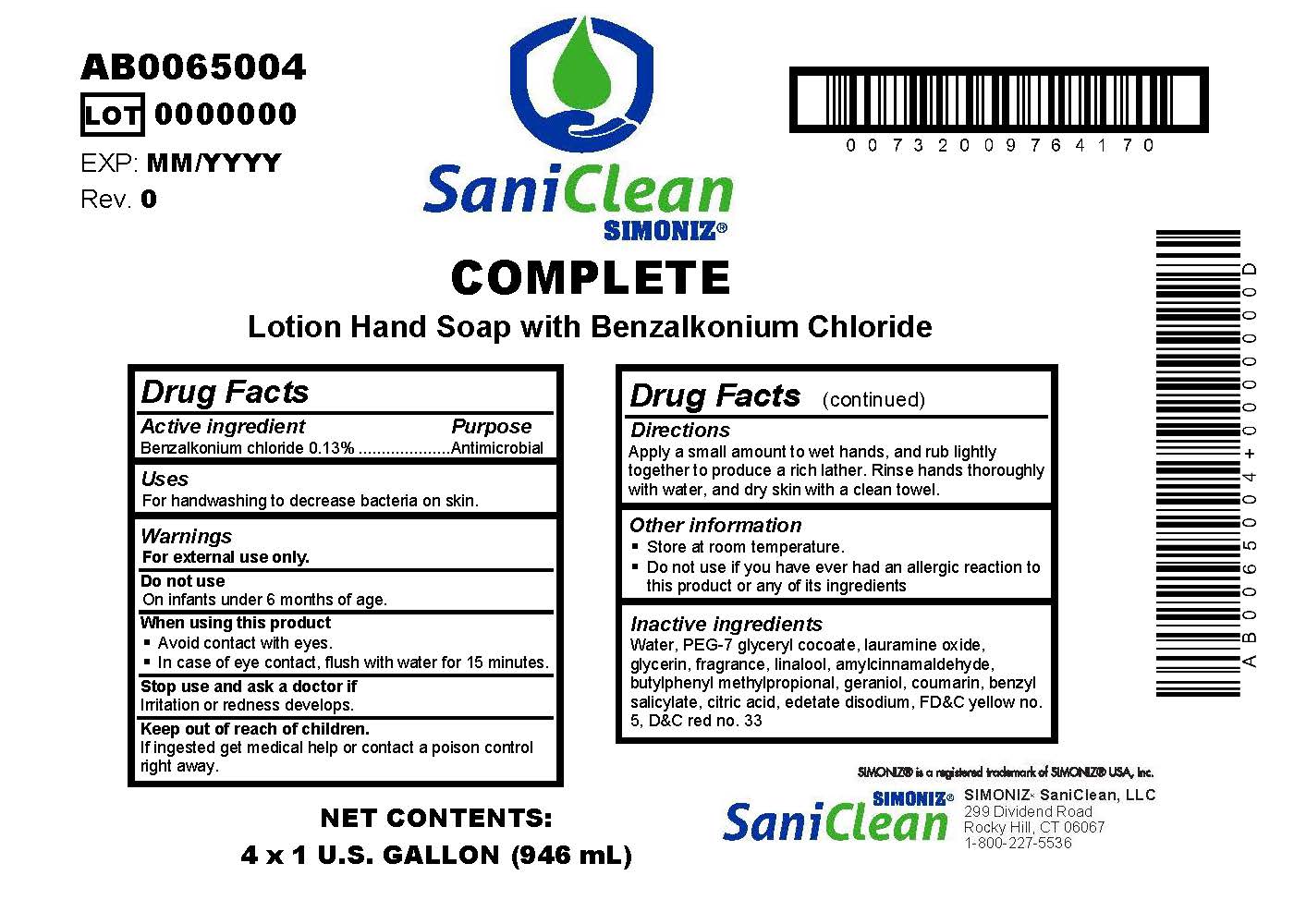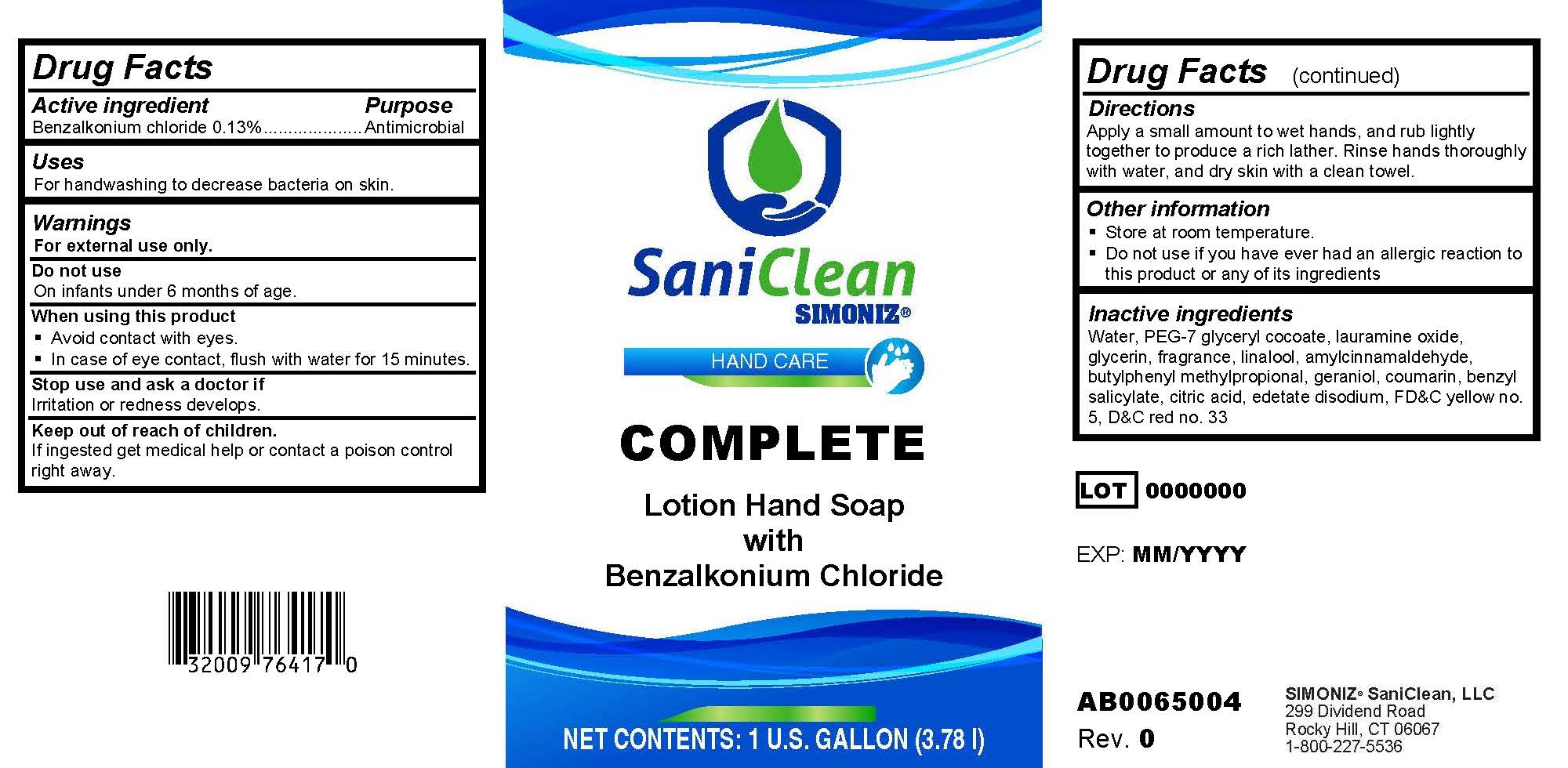 DRUG LABEL: Complete
NDC: 63900-101 | Form: SOAP
Manufacturer: Simoniz Saniclean, LLC
Category: otc | Type: HUMAN OTC DRUG LABEL
Date: 20251027

ACTIVE INGREDIENTS: BENZALKONIUM CHLORIDE 0.13 g/100 mL
INACTIVE INGREDIENTS: LAURAMINE OXIDE; GLYCERIN; .ALPHA.-AMYLCINNAMALDEHYDE; GERANIOL; WATER; BUTYLPHENYL METHYLPROPIONAL; BENZYL SALICYLATE; COUMARIN; FD&C YELLOW NO. 5; D&C RED NO. 33; ANHYDROUS CITRIC ACID; LINALOOL, (+/-)-; EDETATE DISODIUM

Complete Lotion Hand Soap with 0.14% Benzalkonium Chloride

Active ingredient

Benzalkonium chloride 0.13%

Purpose

Antimicrobial

Uses

For handwashing to decrease bacteria on skin.

Warnings

For external use only.

Do not use

On infants under 6 months of age.

When using this product

- Avoid contact with eyes.
- In case of eye contact, flush with water for 15 minutes.

Stop use and ask a doctor if

Irritation or redness develops.

Keep out of reach of children.

If swallowed, drink a large quantity of water and seek medical help or contact a poison control center.

Directions

Apply a small amount to wet hands, and rub lightly together to produce a rich lather. Rinse hands thoroughly with water, and dry skin with a clean towel.

Other Information

- Store at room temperature.
- Do not use if you have ever had an allergic reaction to this product or any of its ingredients

Inactive ingredients
water; PEG-7 glyceryl cocoate; lauramine oxide; glycerin; fragrance (linalool, (+/-)-; .alpha.-amylcinnamaldehyde; butylphenyl methylpropional; geraniol; coumarin; benzyl salicylate); anhydrous citric acid; edetate disodium; FD&C yellow no. 5; D&C red no. 33

LOT

EXP:

Simoniz Saniclean, LLC

299 Dividend Road

Rocky Hill, CT 06067

1-800-227-5536

PACKAGE LABEL

SaniClean

SIMONIZ

HAND CARE

Complete

Lotion Hand Soap

with

Benzalkonium Chloride

NET CONTENTS: 1 U.S. gallon (378 l)